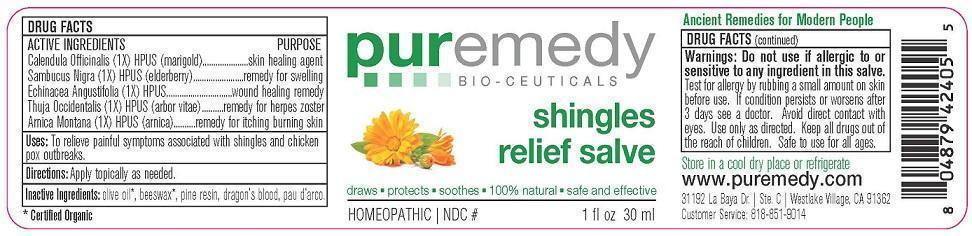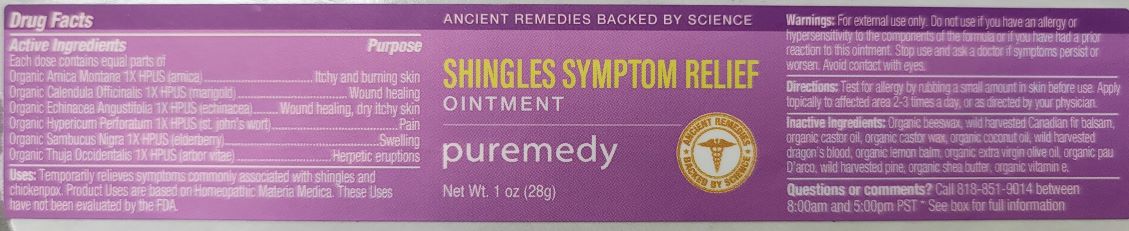 DRUG LABEL: SHINGLES RELIEF
NDC: 52810-402 | Form: SALVE
Manufacturer: PUREMEDY
Category: homeopathic | Type: HUMAN OTC DRUG LABEL
Date: 20240111

ACTIVE INGREDIENTS: CALENDULA OFFICINALIS FLOWER 1 [hp_X]/100 mL; SAMBUCUS NIGRA FLOWER 1 [hp_X]/100 mL; ECHINACEA ANGUSTIFOLIA 1 [hp_X]/100 mL; THUJA OCCIDENTALIS LEAF 1 [hp_X]/100 mL; ARNICA MONTANA 1 [hp_X]/100 mL
INACTIVE INGREDIENTS: OLIVE OIL; YELLOW WAX; PINE NEEDLE OIL (PINUS SYLVESTRIS); DRAGON'S BLOOD; TABEBUIA IMPETIGINOSA LEAF

SHINGLES RELIEF (52810-402)

ACTIVE INGREDIENTS

CALENDULA OFFICINALIS (1X) HPUS) (MARIGOLD)

SAMBUCUS NIGRA (1X) HPUS (ELDER BARK AND FLOWER)

ECHINACEA ANGUSTIFOLIA (1X) HPUS (ECHINACEA)

THUJA OCCIDENTALIS (1X) HPUS (ARBOR VITAE)

ARNICA MONTANA (1X) HPUS (ARNICA)

PURPOSE

SKIN HEALING AGENT

REMEDY FOR SWELLING

WOUND HEALING REMEDY

REMEDY FOR HERPES ZOSTER

REMEDY FOR ITCHING BURNING SKIN

INDICATIONS AND USAGE

USES: TO RELIEVE PAINFUL SYMPTOMS ASSOCIATED WITH SHINGLES AND CHICKEN POX OUTBREAKS.

DOSAGE AND ADMINISTRATION

DIRECTIONS: APPLY TOPICALLY AS NEEDED

INACTIVE INGREDIENT

INACTIVE INGREDIENTS: ORG. OLIVE OIL, BEESWAX, PINE RESIN, DRAGON'S BLOOD, PAU D'ARCO

WARNINGS

WARNINGS: DO NOT USE IF ALLERGIC TO OR SENSITIVE TO ANY INGREDIENT IN THIS SALVE. TEST FOR ALLERGY BY RUBBING A SMALL AMOUNT ON SKIN BEFORE USE. IF CONDITION PERSISTS OR WORSENS AFTER 3 DAYS SEE A DOCTOR. AVOID DIRECT CONTACT WITH EYES. USE ONLY AS DIRECTED. KEEP ALL DRUGS OUT OF USE OF CHILDREN. SAFE TO USE FOR ALL AGES.

KEEP ALL DRUGS OUT OF REACH OF CHILDREN.

STORAGE AND HANDLING

STORE IN A COOL DRY PLACE OR REFRIGERATE.

QUESTIONS

CUSTOMER SERVICE 818-851-9014